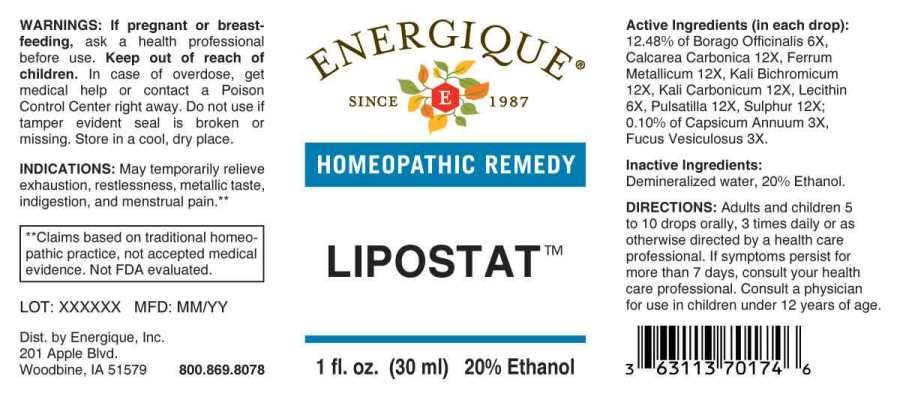 DRUG LABEL: Lipostat
NDC: 44911-0358 | Form: LIQUID
Manufacturer: Energique, Inc.
Category: homeopathic | Type: HUMAN OTC DRUG LABEL
Date: 20241028

ACTIVE INGREDIENTS: CAPSICUM 3 [hp_X]/1 mL; FUCUS VESICULOSUS 3 [hp_X]/1 mL; BORAGE 6 [hp_X]/1 mL; EGG PHOSPHOLIPIDS 6 [hp_X]/1 mL; OYSTER SHELL CALCIUM CARBONATE, CRUDE 12 [hp_X]/1 mL; IRON 12 [hp_X]/1 mL; POTASSIUM DICHROMATE 12 [hp_X]/1 mL; POTASSIUM CARBONATE 12 [hp_X]/1 mL; PULSATILLA PRATENSIS WHOLE 12 [hp_X]/1 mL; SULFUR 12 [hp_X]/1 mL
INACTIVE INGREDIENTS: WATER; ALCOHOL

DRUG FACTS:

ACTIVE INGREDIENTS:

(in each drop): 12.48% of Borago Officinalis 6X, Calcarea Carbonica 12X, Ferrum Metallicum 12X, Kali Bichromicum 12X, Kali Carbonicum 12X, Lecithin 6X, Pulsatilla (Pratensis) 12X, Sulphur 12X; 0.10% of Capsicum Annuum 3X, Fucus Vesiculosus 3X.

INDICATIONS:

May temporarily relieve exhaustion, restlessness, metallic taste, indigestion, and menstrual pain.**

**Claims based on traditional homeopathic practice, not accepted medical evidence. Not FDA evaluated.

WARNINGS:

If pregnant or breastfeeding, ask a health professional before use.

Keep out of reach of children. In case of overdose, get medical help or contact a Poison Control Center right away.

Do not use if tamper evident seal is broken or missing.

Store in a cool, dry place.

Keep out of reach of children. In case of overdose, get medical help or contact a Poison Control Center right away.

DIRECTIONS:

Adults and children 5 to 10 drops orally, 3 times daily or as otherwise directed by a health care professional. If symptoms persist for more than 7 days, consult your health care professional. Consult a physician for use in children under 12 years of age.

INDICATIONS:

May temporarily relieve exhaustion, restlessness, metallic taste, indigestion, and menstrual pain.**

**Claims based on traditional homeopathic practice, not accepted medical evidence. Not FDA evaluated.

INACTIVE INGREDIENTS:

Demineralized water, 20% Ethanol.

QUESTIONS:

Dist. by Energique, Inc.

201 Apple Blvd.

Woodbine, IA 51579 800.869.8078

PACKAGE LABEL DISPLAY:

ENERGIQUE

SINCE 1987

HOMEOPATHIC REMEDY

LIPOSTAT

1 fl. oz. (30 ml)